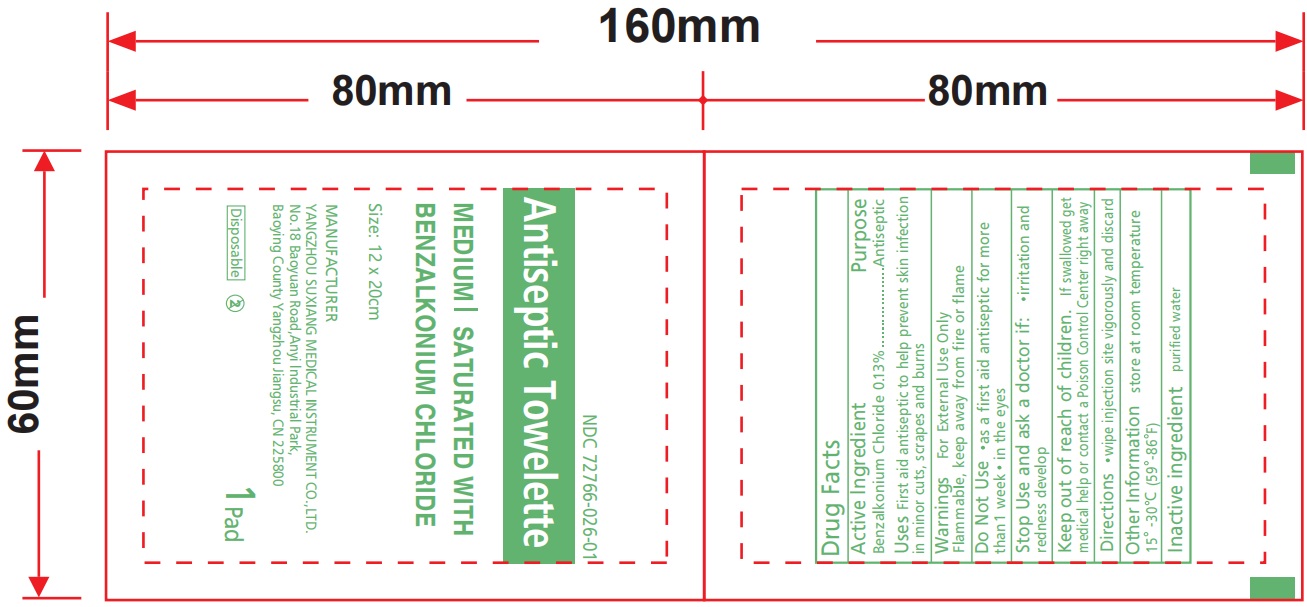 DRUG LABEL: Benzalkonium Chloride Antiseptic Towelette
NDC: 72766-026 | Form: CLOTH
Manufacturer: Yangzhou Suxiang Medical Instrument Co., Ltd.
Category: otc | Type: HUMAN OTC DRUG LABEL
Date: 20240306

ACTIVE INGREDIENTS: BENZALKONIUM CHLORIDE 1.26 g/1 1
INACTIVE INGREDIENTS: WATER

Benzalkonium Chloride Towelette

Active Ingredient

Benzalkonium Chloride, 0.13%

Purpose

First Aid Antiseptic

Uses

First Aid Antiseptic

Warnings

For External Use Only

Do Not Use

For deep puncture wounds, animal bites or serious burns

In the eyes

Over large areas of the body

Stop Use and ask a doctor if

if irritation and redness develops and persists for more than 72 hours

Keep out of reach of children

If swallowed, get medical help or contact a Poison Control Center right away.

Directions

Open packet and use as a washcloth.

As a first aid antiseptic

Clean affected area

Apply 1 to 3 times daily

May be covered with a sterile bandage

If bandaged, let dry first

Other Information

Store at room temperature

Avoid excessive heat

Inactive Ingredients

Purified Water